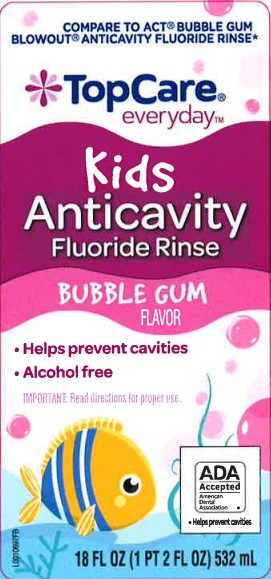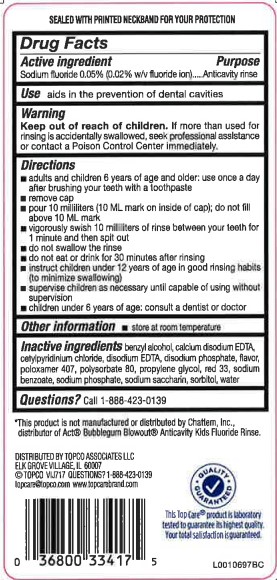 DRUG LABEL: Anticavity Fluoride Rinse
NDC: 36800-004 | Form: RINSE
Manufacturer: Topco Associates LLC
Category: otc | Type: HUMAN OTC DRUG LABEL
Date: 20260213

ACTIVE INGREDIENTS: SODIUM FLUORIDE 0.2 mg/1 mL
INACTIVE INGREDIENTS: BENZYL ALCOHOL; EDETATE CALCIUM DISODIUM; CETYLPYRIDINIUM CHLORIDE; EDETATE DISODIUM; SODIUM ACID PYROPHOSPHATE; POLOXAMER 407; POLYSORBATE 80; PROPYLENE GLYCOL; D&C RED NO. 33; SODIUM BENZOATE; SODIUM PHOSPHATE; SACCHARIN SODIUM; SORBITOL; WATER

Top Care 004.002/004AE
Anticavity Fluoride Rinse, Bubble Gum

Tamper Evident Statement

SEALED WITH PRINTED NECKBAND FOR YOUR PROTECTION

Active ingredient

Sodium fluoride 0.05% (0.02% w/v fluoride ion)

PURPOSE

Anticavity rinse

Use

aids in the prevention of dental cavities

Warnings

for this product

Keep out of reach of children.

If more than used for rinsing is accidentally swallowed, seek professional assistance or contact a Poison Control Center immediately.

Directions

- adults and children 6 years of age and older: use once a day after brushing your teeth with a toothpaste
- remove cap
- pour 10 milliters (10 mL mark on inside of cap): do not fill above the 10 mL mark
- vigorously swish 10 milliliters of rinse between your teeth for 1 minute and then spit out
- do not swallow the rinse
- do not eat or drink for 30 minutes after rinsing
- instruct children under 12 years of age in good rinsing habits (to minimize swallowing)
- do not swallow the rinse
- do not eat or drink for 30 minutes after rinsing
- instruct children under 12 years of age in good rinsing habits (to minimize swallowing)
- supervise children as necessary until capable of using without supervision
- children under 6 years of age: consult a dentist or doctor

Other information

- store at room temperature

Inactive ingredients

benzyl alcohol, calcium disodium EDTA, cetylpyridinium chloride, disodium EDTA, disodium phosphate, flavor, poloxamer 407, polysorbate 80, propylene glycol, red 33, sodium benzoate, sodium phosphate, sodium saccharin, sorbitol, water

Disclaimer

*This product is not manufactured or distributed by Chattem, Inc., distributor of Act® Bubblegum Blowout®Anticavity Kids Fluoride Rinse.

ADVERSE REACTION

Distributed by: TOPCO ASSOCIATES LLC

ELK GROVE VILLAGE, IL 60007

©TOPCO VIJ717 QUESTIONS? 1-888-423-0139

topcare@topco.com www.topcarebrand.com

QUALITY GUARANTEED

This Top Care product is laboratory tested to guarantee its highest quality. Your satisfaction is guaranteed.

principal display panel

COMPARE TO ACT®BUBBLE GUM BLOWOUT®ANTICAVITY FLUORIDE RINSE*

TOP CARE®

everyday™

Kids

Anticavity

Fluoride Rinse

BUBBLE GUM

FLAVOR

- Helps prevent cavities
- Alcohol free

IMPORTANT: READ DIRECTIONS FOR PROPER USE.

ADA Accepted

American Dental Association

- Helps prevent cavities

18 FL OZ (1 PT 2 FL OZ) 532 mL